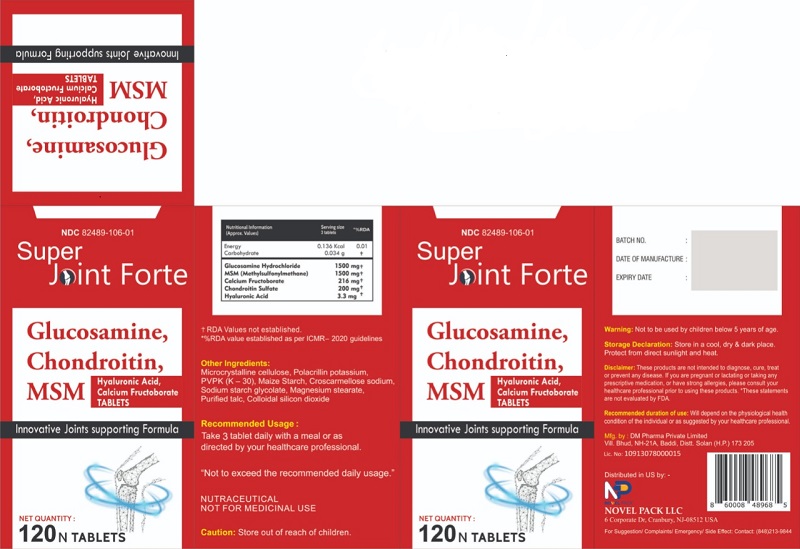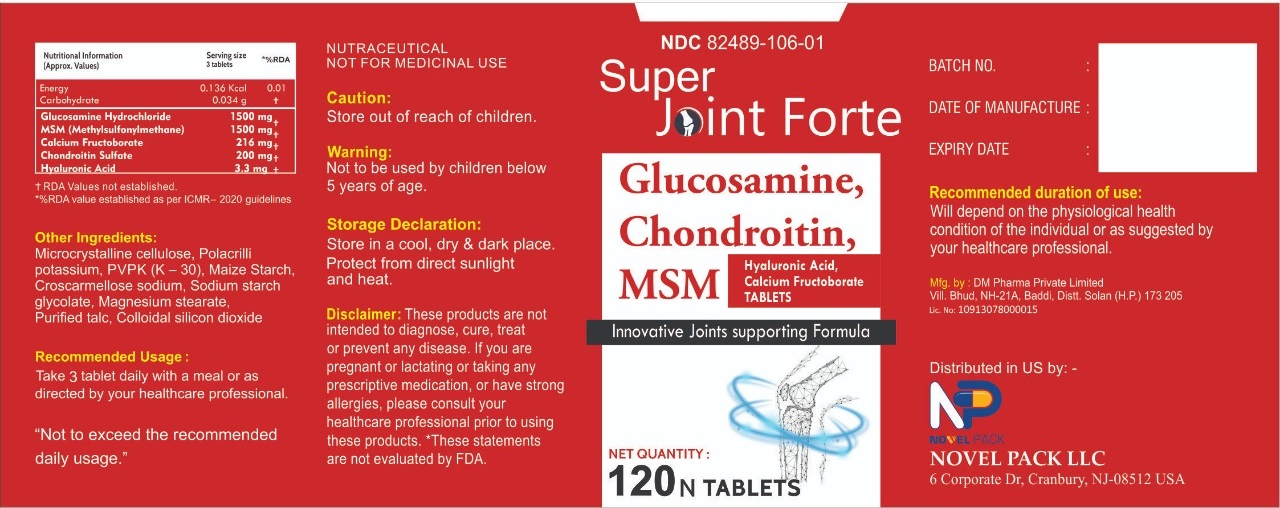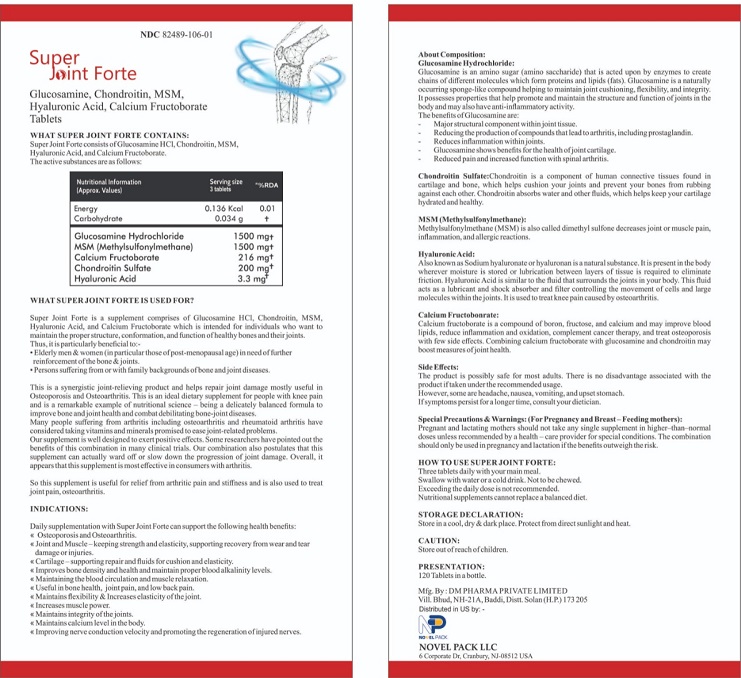 DRUG LABEL: Super Joint Forte
NDC: 82489-106 | Form: TABLET
Manufacturer: Novel Pack LLC
Category: other | Type: Dietary Supplement
Date: 20220505

ACTIVE INGREDIENTS: GLUCOSAMINE HYDROCHLORIDE 1500 mg/1 1; DIMETHYL SULFONE 1500 mg/1 1; CALCIUM FRUCTOBORATE 216 mg/1 1; CHONDROITIN 6-SULFATE 200 mg/1 1; HYALURONIC ACID 3.3 mg/1 1
INACTIVE INGREDIENTS: MICROCRYSTALLINE CELLULOSE; POLACRILIN POTASSIUM; POVIDONE K30; STARCH, CORN; SODIUM STARCH GLYCOLATE TYPE A; MAGNESIUM STEARATE; TALC; SILICON DIOXIDE

SUPER JOINT FORTE
Glucosamine, Chondroitin, MSM, Hyaluronic Acid, Calcium Fructoborate Tablets

STATEMENT OF IDENTITY

SUPER JOINT FORTE
Glucosamine, Chondroitin, MSM, Hyaluronic Acid, Calcium Fructoborate Tablets

Innovative Joints Supporting Formula

Dosage

Take 3 tablet daily with a meal or as directed by your healthcare professional.

"Not to exceed the recommended daily usuage."

Storage Declaration

Store in a cool, dry & dark place. Protect from direct sunlight and heat.

WARNINGS

Not to be used by children below 5 years of age.

Store out of rech of children